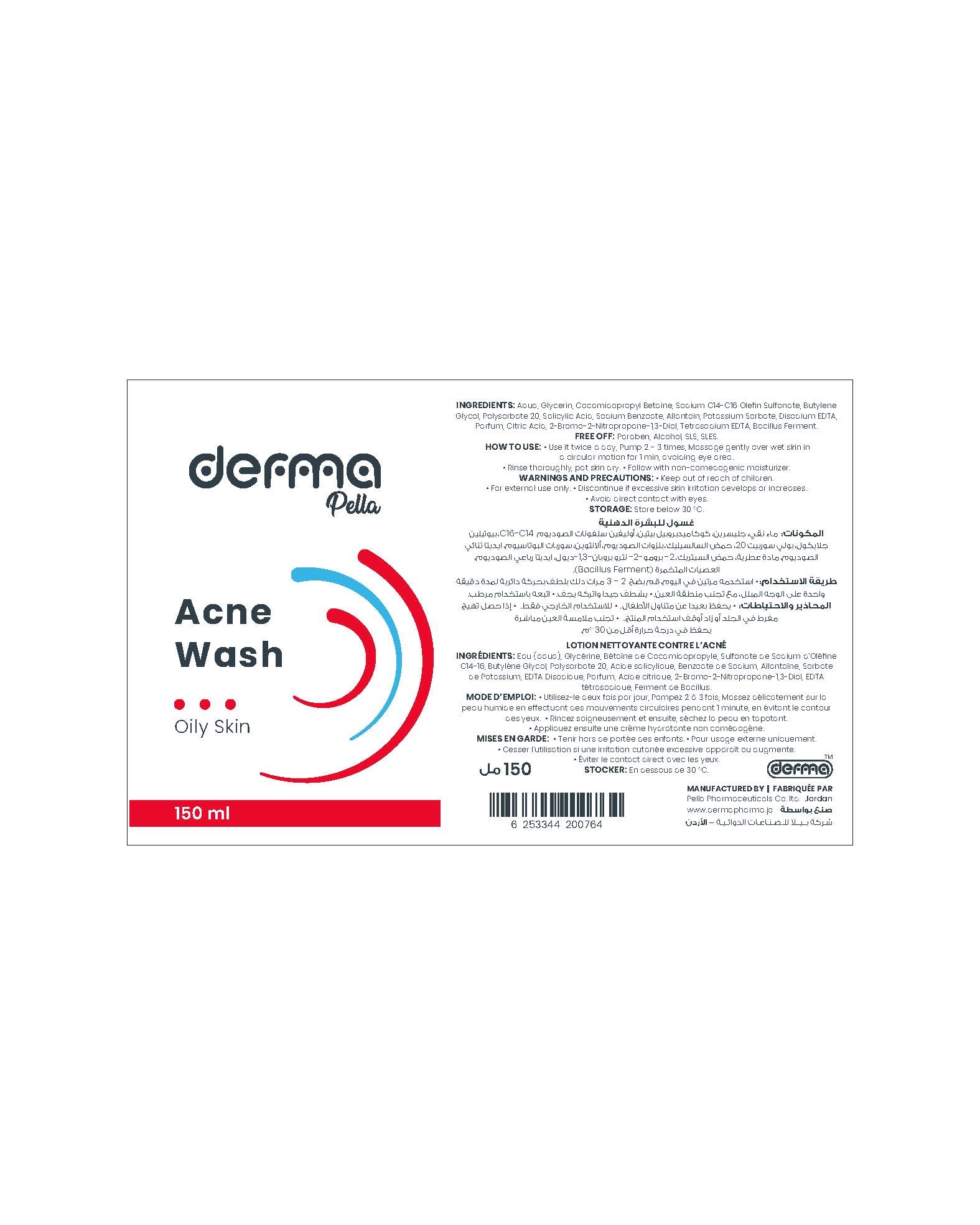 DRUG LABEL: Derma Pella Acne Wash for Oily Skin
NDC: 82160-764 | Form: SOLUTION
Manufacturer: Pella Pharmaceuticals Co. Ltd
Category: otc | Type: HUMAN OTC DRUG LABEL
Date: 20250121

ACTIVE INGREDIENTS: SALICYLIC ACID 5 mg/1 mL
INACTIVE INGREDIENTS: BUTYLENE GLYCOL; POTASSIUM SORBATE; EDETATE DISODIUM ANHYDROUS; BRONOPOL; SODIUM C14-16 OLEFIN SULFONATE; WATER; POLYSORBATE 20; ALLANTOIN; SODIUM BENZOATE; EDETATE SODIUM; GLYCERIN; COCAMIDOPROPYL BETAINE; CITRIC ACID MONOHYDRATE

Acne Wash

Forms and Presentation

Solution: Plastic Bottle, 150 ml

Active Ingredient

Salicylic Acid

Inactive Ingredients

Aqua, Glycerin, Cocamidopropyl Betain, Sodium C14-16 Olefin Sulfonate, Butylene Glycol, Polysorbate 20, Sodium Benzoate, Allantoin, Potassium Sorbate, Disodium EDTA, Parfum, Citric Acid, 2-Bromo-2-Nitropropane-1,3-Diol, Tetrasodium EDTA, Bacillus Ferment

Purpose

Facial Cleanser for Oily Skin

Properties

A lightweight, translucent, water-based Alcohol and Sulfate free facial foaming cleanser.

This product contains a beta hydroxyl acid (BHA) which is a salicylic acid that helps remove dead skin cells, reduce blackheads and the appearance of pores, so it prevents acne.

And also it contains Bacillus Ferment which is a multifunctional biotechnological ingredient obtains from microorganism isolated from natural clay, offers a cleaner smother and more beautiful skin by:

- P. acne biofilm inhibition.
- Reduced inflammatory response to P. acne.
- Skin regenerating effect.
- Cleansing activity.
- Antioxidant response determined by reactive oxygen species (ROS).

Also it contains Allantoin which is an effective moisturizing ingredient used for it is gentle and non-irritating qualities.

Paraben free, Alcohol free, SLS free, SLES free.

Indications

Non-irritating foaming cleanser formulated for acne-prone skins, helps gently exfoliate skin without over drying, deep cleans pores control excess oil, unclog pores and prevent new acne from forming.

Precautions

Keep out of reach of children

Warnings

- For external use only.
- Discontinue if excessive skin irritation develops or increases. If irritation persists, consult with a physician or pharmacist.
- Avoid direct contact with eyes, if contact occurs, rinse thoroughly with water.

Contraindications

Hypersensitivity to any of the components.

Side Effects

It is well tolerated product but mild irritation, dryness, redness may occur.

Dosage and Administration

- Use it twice a day, morning and night.
- Pump 2 - 3 times onto the tips of your fingers.
- Massage gently over wet skin in a circular motion for 1 min, avoiding eye area.
- Rinse thoroughly, pat skin dry.
- Follow with non comedogenic moisturizer.
- If excessive dryness or peeling occurs, reduce usage.

Storage Conditions

Store below 30◦C.